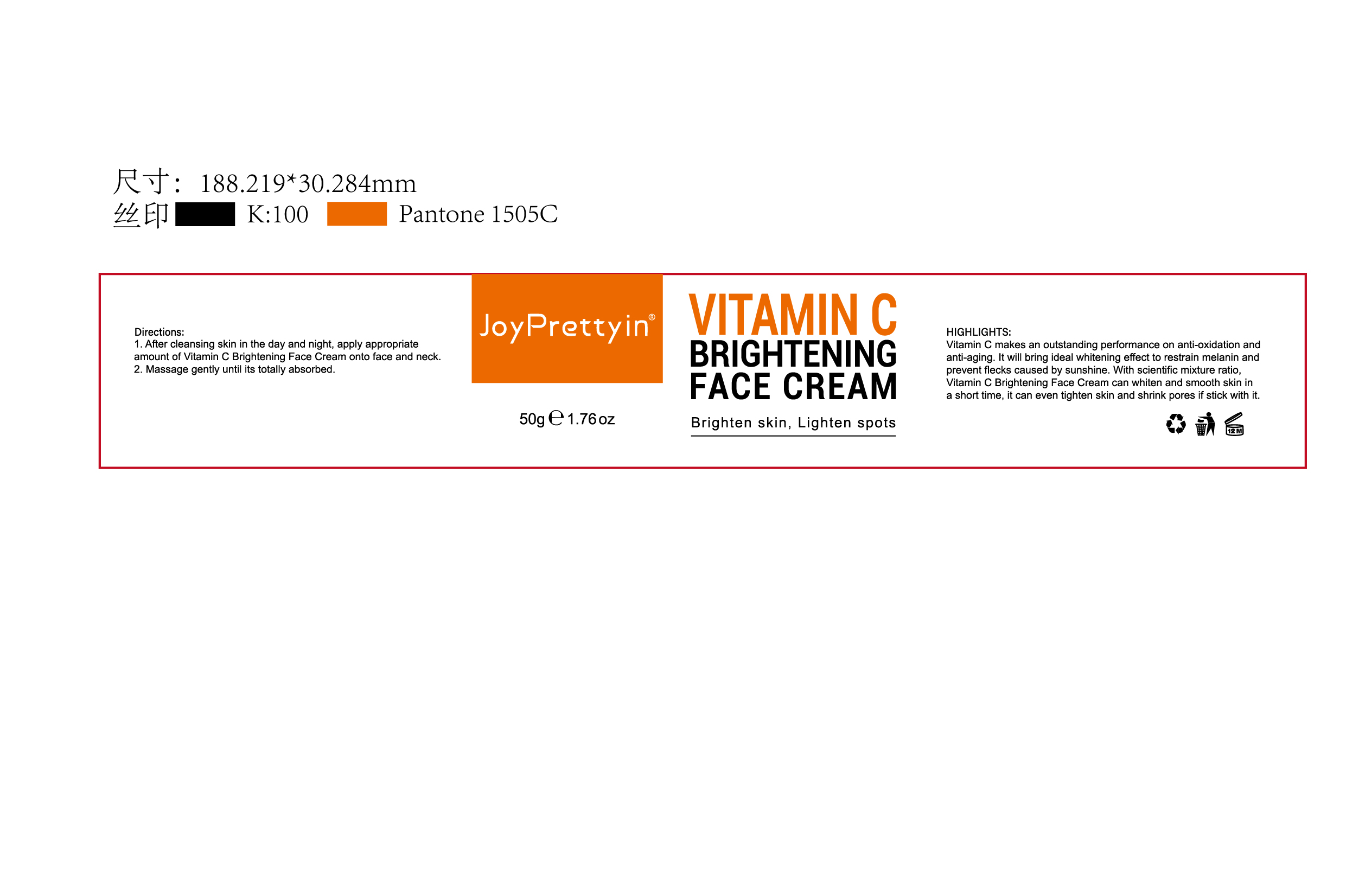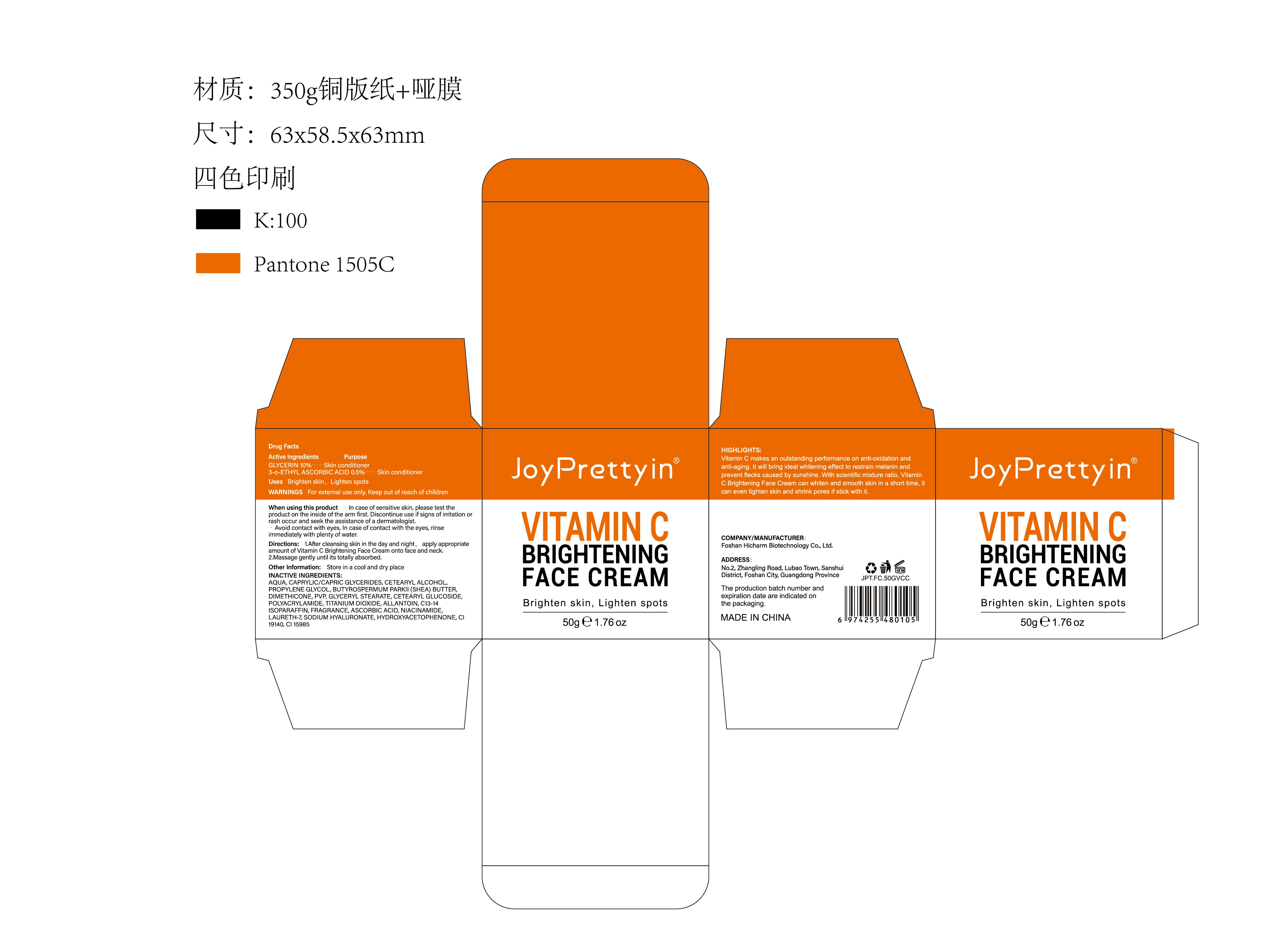 DRUG LABEL: Joypretty Vitamin C Brightening Face Cream
NDC: 84186-018 | Form: CREAM
Manufacturer: Guangzhou Bonnieco Cosmetics Co., Ltd
Category: otc | Type: HUMAN OTC DRUG LABEL
Date: 20240528

ACTIVE INGREDIENTS: CAPRYLIC/CAPRIC ACID 5 g/100 g
INACTIVE INGREDIENTS: WATER; PROPYLENE; CETOSTEARYL ALCOHOL; ETHYLENE GLYCOL; GLYCERIN; DIMETHICONE; GLYCERYL MONOSTEARATE; TITANIUM DIOXIDE; ASCORBIC ACID; HYALURONATE SODIUM; C13-16 ISOPARAFFIN; BUTTER; VITELLARIA PARADOXA WHOLE; ALLANTOIN; C13-14 ISOPARAFFIN; FRAGRANCE 13576; FD&C YELLOW NO. 5; POVIDONE; CETEARYL GLUCOSIDE; NIACINAMIDE; HYDROXYACETOPHENONE; FD&C YELLOW NO. 6; PROFENAMINE HIBENZATE; LAURETH-7; POLYACRYLAMIDE (10000 MW)

84186-018

Active Ingredient

CAPRYLIC/CAPRIC 5%

Purpose

face (body part)

Use

1.After cleansing skin in the day and night, apply appropriate amount of Vitamin C Brightening Face Cream onto face and neck.
2.Massage gently until its totally absorbed.

Warnings

For external use only. Keep out of reach of children

Do not use

·in case of sensitive skin, please test the product on the inside of the arm first, Discontinue use if signs of irritation or rash occur and seek the assistance of a dermatologist.
*Avoid contact with eyes, In case of contact with the eyes, rinse immediately with plenty of water.

When Using

In case of contact with the eyes, rinse immediately with plenty of water.

Stop Use

If discomfort arises, please immediately stop using the product and seek the assistance of a dermatologist.

Ask Doctor

If discomfort arises, please immediately stop using the product and seek the assistance of a dermatologist.

Keep Oot Of Reach Of Children

Directions

1.After cleansing skin in the day and night, apply appropriate amount of Vitamin C Brightening Face Cream onto face and neck.
2.Massage gently until its totally absorbed.

Inactive ingredients

AQUA, CAPRYLIC/CAPRIC GLYCERIDES, CETEARYL ALCOHOL, PROPYLENE GLYCOL,BUTYROSPERMUM PARKII (SHEA) BUTTER, DIMETHICONE,PVP, GLYCERYL STEARATE, CETEARYL GLUCOSIDE, POLYACRYLAMIDE,TITANIUM DIOXIDE,ALLANTOIN, C13-14 ISOPARAFFIN,FRAGRANCE,ASCORBIC ACID, NIACINAMIDE LAURETH-7, SODIUM HYALURONATE,HYDROXYACETOPHENONE,CI 19140,CI15985